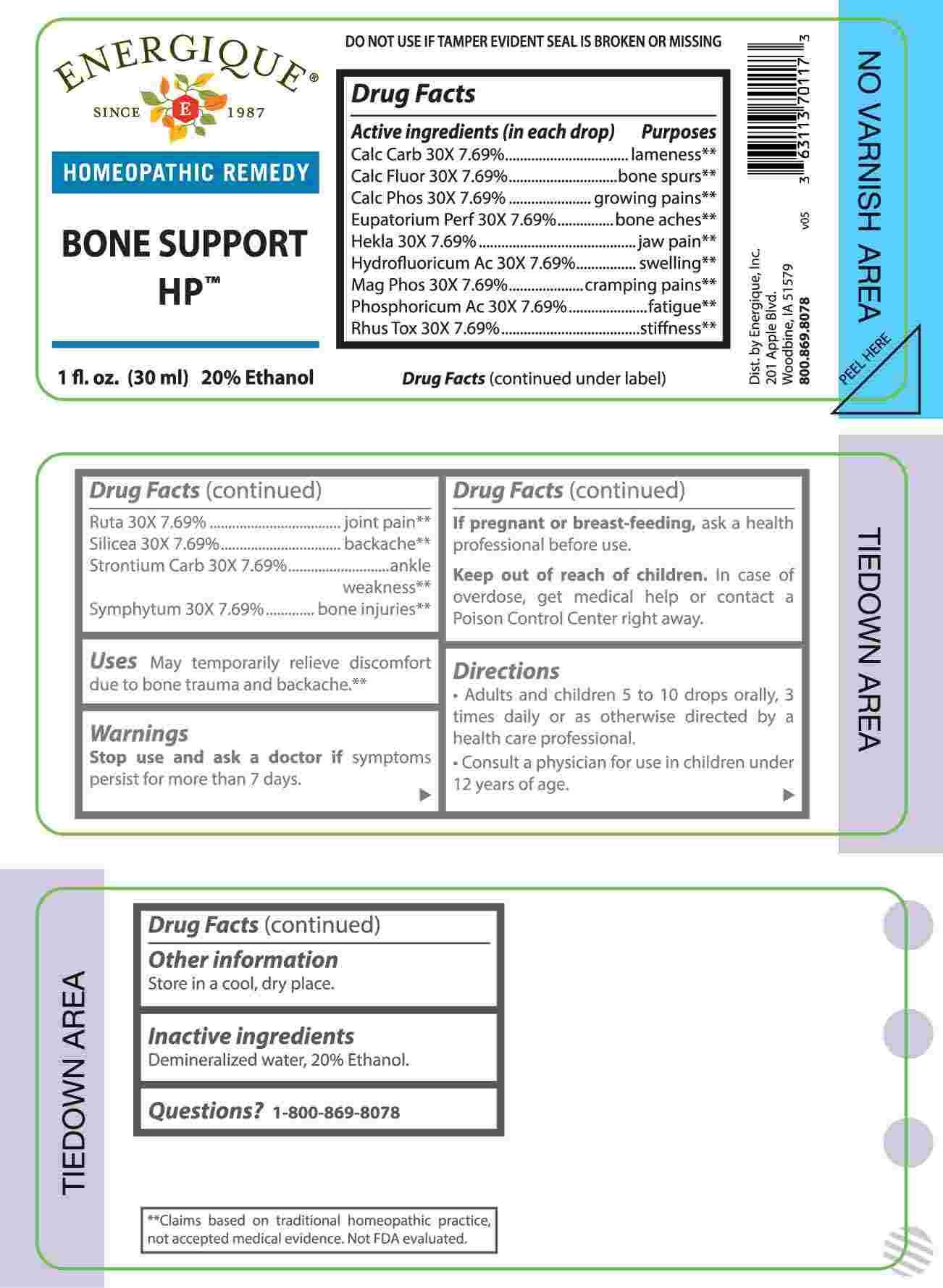 DRUG LABEL: Bone Support
NDC: 44911-0663 | Form: LIQUID
Manufacturer: Energique, Inc.
Category: homeopathic | Type: HUMAN OTC DRUG LABEL
Date: 20240930

ACTIVE INGREDIENTS: OYSTER SHELL CALCIUM CARBONATE, CRUDE 30 [hp_X]/1 mL; CALCIUM FLUORIDE 30 [hp_X]/1 mL; TRIBASIC CALCIUM PHOSPHATE 30 [hp_X]/1 mL; EUPATORIUM PERFOLIATUM FLOWERING TOP 30 [hp_X]/1 mL; HEKLA LAVA 30 [hp_X]/1 mL; HYDROFLUORIC ACID 30 [hp_X]/1 mL; MAGNESIUM PHOSPHATE, DIBASIC TRIHYDRATE 30 [hp_X]/1 mL; PHOSPHORIC ACID 30 [hp_X]/1 mL; TOXICODENDRON PUBESCENS LEAF 30 [hp_X]/1 mL; RUTA GRAVEOLENS FLOWERING TOP 30 [hp_X]/1 mL; SILICON DIOXIDE 30 [hp_X]/1 mL; STRONTIUM CARBONATE 30 [hp_X]/1 mL; COMFREY ROOT 30 [hp_X]/1 mL
INACTIVE INGREDIENTS: WATER; ALCOHOL

DRUG FACTS:

ACTIVE INGREDIENTS:

(in each drop): Calcarea Carbonica 30X 7.69%, Calcarea Fluorica 30X 7.69%, Calcarea Phosphorica 30X 7.69%, Eupatorium Perfoliatum 30X 7.69%, Hekla Lava 30X 7.69%, Hydrofluoricum Acidum 30X 7.69%, Magnesia Phosphorica 30X 7.69%, Phosphoricum Acidum 30X 7.69%, Rhus Tox 30X 7.69%, Ruta Graveolens 30X 7.69%, Silicea 30X 7.69%, Strontium Carbonicum 30X 7.69%, Symphytum Officinale 30X 7.69%.

PURPOSE:

Calcarea Carbonica - lameness,** Calcarea Fluorica – bone spurs,** Calcarea Phosphorica – growing pains,** Eupatorium Perfoliatum – bone aches,** Hekla Lava – jaw pain,** Hydrofluoricum Acidum - swelling,** Magnesia Phosphorica – cramping pains,** Phosphoricum Acidum - fatigue,** Rhus Tox - stiffness,** Ruta Graveolens – joint pain,** Silicea - backache,** Strontium Carbonicum – ankle weakness,** Symphytum Officinale – bone injuries.**

**Claims based on traditional homeopathic practice, not accepted medical evidence. Not FDA evaluated.

USES:

May temporarily relieve discomfort due to bone trauma and backache.**

**Claims based on traditional homeopathic practice, not accepted medical evidence. Not FDA evaluated.

WARNINGS:

Stop use and ask a doctor if symptons persist for more than 7 days.

If pregnant or breast-feeding, ask a health professional before use.

Keep out of reach of children. In case of overdose, get medical help or contact a Poison Control Center right away.

DO NOT USE IF TAMPER EVIDENT SEAL IS BROKEN OR MISSING

Store in a cool, dry place.

KEEP OUT OF REACH OF CHILDREN:

In case of overdose, get medical help or contact a Poison Control Center right away.

DIRECTIONS:

• Adults and children 5 to 10 drops orally, 3 times daily or as otherwise directed by a health care professional.

• Consult a physician for use in children under 12 years of age.

INACTIVE INGREDIENTS:

Demineralized water, 20% Ethanol.

QUESTIONS:

Dist. by Energique, Inc.

201 Apple Blvd

Woodbine, IA 51579

800.869.8078

PACKAGE LABEL DISPLAY:

ENERGIQUE

SINCE 1987

HOMEOPATHIC REMEDY

BONE SUPPORT HP

1 fl. oz. (30 ml)